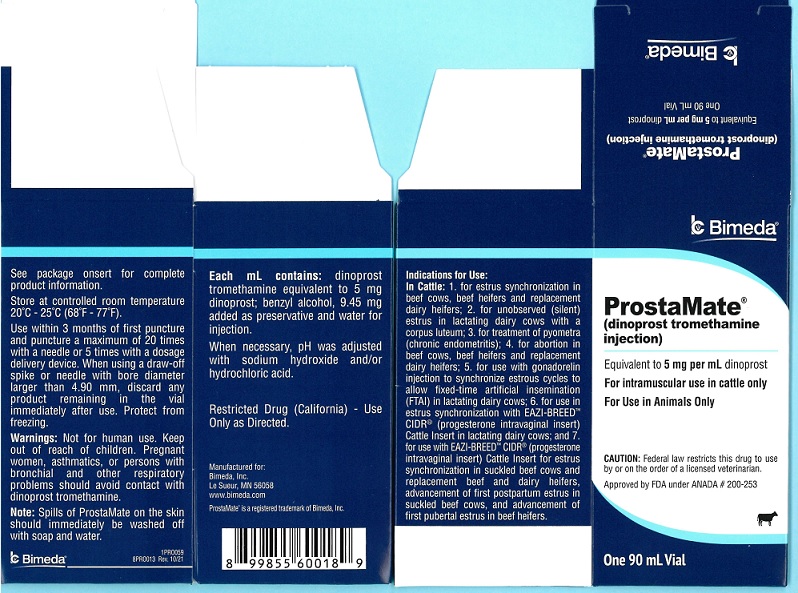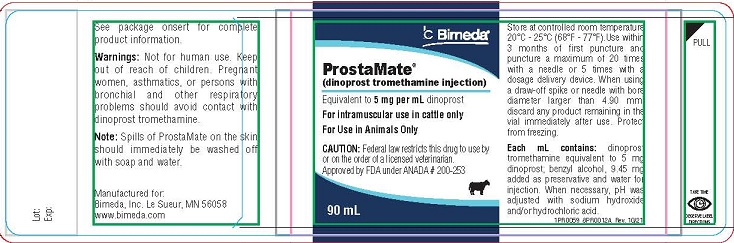 DRUG LABEL: ProstaMate
NDC: 61133-4001 | Form: INJECTION, SOLUTION
Manufacturer: Bimeda, Inc.
Category: animal | Type: PRESCRIPTION ANIMAL DRUG LABEL
Date: 20241030

ACTIVE INGREDIENTS: DINOPROST TROMETHAMINE 5 mg/1 mL
INACTIVE INGREDIENTS: BENZYL ALCOHOL 9.45 mg/1 mL

ProstaMate™
(dinoprost tromethamine)
Sterile Solution

DESCRIPTION

CAUTION

Federal law restricts this drug to use by or on the order of a licensed veterinarian.

ProstaMate®

(dinoprost tromethamine injection)

5 mg dinoprost/mL as dinoprost tromethamine

DESCRIPTION

ProstaMate (5 mg dinoprost/mL) is a sterile solution containing the naturally occurring prostaglandin F2 alpha (dinoprost) as the tromethamine salt. Each mL contains dinoprost tromethamine equivalent to 5 mg dinoprost: also, benzyl alcohol, 9.45 mg added as preservative and water for injection.

When necessary, pH was adjusted with sodium hydroxide and/or hydrochloric acid. Dinoprost tromethamine is a white or slightly off-white crystalline powder that is readily soluble in water at room temperature in concentrations to at least 200 mg/mL.

INDICATIONS AND USAGE

Cattle

ProstaMate is indicated as a luteolytic agent. ProstaMate is effective only in those cattle having a corpus luteum, i.e., those which ovulated at least five days prior to treatment.

Future reproductive performance of animals that are not cycling will be unaffected by injection of ProstaMate.

For estrus synchronization in beef cows, beef heifers and replacement dairy heifers

For unobserved (silent) estrus in lactating dairy cows with a corpus luteum

For treatment of pyometra (chronic endometritis) in cattle

For abortion in beef cows, beef heifers and replacement dairy heifers

For use with gonadorelin injection to synchronize estrous cycles to allow fixed-time artificial insemination (FTAI) in lactating dairy cows

For use with EAZI-BREEDTM CIDR® (progesterone intravaginal insert) Cattle Insert for synchronization of estrus in lactating dairy cows

For use with EAZI-BREEDTM CIDR® (progesterone intravaginal insert) Cattle Insert for synchronization of estrus in suckled beef cows and replacement beef and dairy heifers, advancement of first postpartum estrus in suckled beef cows, and advancement of first pubertal estrus in beef heifers

Swine

For parturition induction in swine

Mares

For controlling the timing of estrus in estrous cycling mares

For difficult-to-breed mares (clinically anestrous mares that have a corpus luteum)

MANAGEMENT CONSIDERATIONS

Many factors contribute to success and failure of reproduction management, and these factors are important also when time of breeding is to be regulated with ProstaMate. Some of these factors are:

Cattle must be ready to breed—they must have a corpus luteum and be healthy;

Nutritional status must be adequate as this has a direct effect on conception and the initiation of estrus in heifers or return of estrous cycles in cows following calving;

Physical facilities must be adequate to allow cattle handling without being detrimental to the animal;

Estrus must be detected accurately if timed AI is not employed;

Semen of high fertility must be used;

Semen must be inseminated properly.

A successful breeding program can employ ProstaMate effectively, but a poorly managed breeding program will continue to be poor when ProstaMate is employed unless other management deficiencies are remedied first. Cattle expressing estrus following ProstaMate are receptive to breeding by a bull. Using bulls to breed large numbers of cattle in heat following ProstaMate will require proper management of bulls and cattle.

DOSAGE AND ADMINISTRATION

As with any multi-dose vial, practice aseptic techniques in withdrawing each dose to decrease the possibility of post-injection bacterial infections. Adequately clean and disinfect the vial stopper prior to entry with a sterile needle and syringe. Use only sterile needles, and use each needle only once.

Use within 3 months of first puncture and puncture a maximum of 20 times with a needle or 5 times with a dosage delivery device. When using a draw-off spike or needle with bore diameter larger than 4.90 mm, discard any product remaining in the vial immediately after use.

Cattle

1. For Estrus Synchronization in Beef Cows, Beef Heifers and Replacement Dairy Heifers. ProstaMate is used to control the timing of estrus and ovulation in estrous cycling cattle that have a corpus luteum. Inject a dose of 5 mL ProstaMate (25 mg dinoprost) intramuscularly either once or twice at a 10 to 12 day interval. With the single injection, cattle should be bred at the usual time relative to estrus. With the two injections cattle can be bred after the second injection either at the usual time relative to detected estrus or at about 80 hours after the second injection of ProstaMate. Estrus is expected to occur 1 to 5 days after injection if a corpus luteum was present. Cattle that do not become pregnant to breeding at estrus on days 1 to 5 after injection will be expected to return to estrus in about 18 to 24 days.

2. For Unobserved (Silent) Estrus in Lactating Dairy Cows with a Corpus Luteum. Inject a dose of 5 mL ProstaMate (25 mg dinoprost) intramuscularly. Breed cows as they are detected in estrus. If estrus has not been observed by 80 hours after injection, breed at 80 hours. If the cow returns to estrus, breed at the usual time relative to estrus.

3. For Treatment of Pyometra (chronic endometritis) in Cattle. Inject a dose of 5 mL ProstaMate (25 mg dinoprost) intramuscularly.

4. For Abortion in Beef Cows, Beef Heifers and Replacement Dairy Heifers. ProstaMate is indicated for its abortifacient effect in beef cows, beef heifers and replacement dairy heifers during the first 100 days of gestation. Inject a dose of 25 mg dinoprost (5 mL) intramuscularly. Cattle that abort will abort within 35 days of injection.

5. For use with gonadorelin injection to synchronize estrous cycles to allow fixed-time artificial insemination (FTAI) in lactating dairy cows: Administer 2 to 4 mL gonadorelin injection (100-200 mcg gonadorelin) per cow as an intramuscular injection in a treatment regimen with the following framework:

• Administer the first dose of gonadorelin injection (2-4 mL) at Day 0

• Administer ProstaMate (25 mg dinoprost, as dinoprost tromethamine) by intramuscular injection 6-8 days after the first dose of gonadorelin injection.

• Administer a second dose of gonadorelin injection (2-4 mL) 30 to 72 hours after the ProstaMate injection.

• Perform FTAI 0 to 24 hours after the second dose of gonadorelin injection, or inseminate cows on detected estrus using standard herd practices.

Below are three examples of treatment regimens for FTAI that fit within the dosage regimen framework described immediately above:

 | Example 1 | Example 2 | Example 3
Day 0; (Monday) | 1st gonadorelin injection | 1st gonadorelin injection | 1st gonadorelin injection
Day 7; (the following Monday | ProstaMate | ProstaMate | ProstaMate
Day 9 (Wednesday) | 2nd gonadorelin injection + FTAI at 48 hours after ProstaMate | 2nd gonadorelin injection at 48 hours after ProstaMate | 2nd gonadorelin injection at 56 hours after ProstaMate
Day 10; (Thursday) |  | FTAI 24 hours after 2nd gonadorelin injection | FTAI 18 hours after 2nd gonadorelin injection

6. For use with EAZI-BREED™ CIDR® (progesterone intravaginal insert) Cattle Insert for Synchronization of Estrus in Lactating Dairy Cows:

• Administer one EAZI-BREEDTM CIDR® Cattle Insert per animal and remove 7 days later (for example if administered on a Monday remove the following Monday).

• Administer 5 mL ProstaMate at the time of removal of the EAZI-BREEDTM CIDR® Cattle Insert.

• Observe animals for signs of estrus on Days 2 to 5 after removal of the EAZI-BREEDTM CIDR® Cattle Insert and inseminate animals found in estrus following normal herd practices.

7. For use with EAZI-BREED™ CIDR® (progesterone intravaginal insert) Cattle Insert for synchronization of estrus in suckled beef cows and replacement beef and dairy heifers, advancement of first postpartum estrus in suckled beef cows, and advancement of first pubertal estrus in beef heifers:

• Administer one EAZI-BREEDTM CIDR® Cattle Insert per animal for 7 days (for example, if administered on a Monday remove on the following Monday).

• Inject 5 mL ProstaMate (equivalent to 5 mg/mL dinoprost) 1 day prior to EAZI-BREEDTM CIDR® Cattle Insert removal, on Day 6 of the 7 day administration period.

• Observe animals for signs of estrus on Days 1 to 3 after removal of the EAZI-BREEDTM CIDR® Cattle Insert and inseminate animals about 12 hours after onset of estrus.

Swine

For Parturition Induction in Swine: For intramuscular use for parturition induction in swine. ProstaMate is indicated for parturition induction in swine when injected within 3 days of normal predicted farrowing. The response to treatment varies by individual animals with a mean interval from administration of 2 mL ProstaMate (10 mg dinoprost) to parturition of approximately 30 hours. This can be employed to control the time of farrowing in sows and gilts in late gestation.
Management Considerations: Several factors must be considered for the successful use of ProstaMate for parturition induction in swine. The product must be administered at a relatively specific time (treatment earlier than 3 days prior to normal predicted farrowing may result in increased piglet mortality). It is important that adequate records be maintained on (1) the average length of gestation period for the animals on a specific location, and (2) the breeding and projected farrowing dates for each animal. This information is essential to determine the appropriate time for administration of ProstaMate.

Mares

ProstaMate is indicated for its luteolytic effect in mares. Administer a single intramuscular injection of 1 mg per 100 lbs (45.5 kg) body weight which is usually 1 mL to 2 mL ProstaMate. This luteolytic effect can be utilized to control the timing of estrus in estrous cycling and clinically anestrous mares that have a corpus luteum in the following circumstances:
1. Controlling Time of Estrus of Estrous Cycling Mares: Mares treated with ProstaMate during diestrus (4 or more days after ovulation) will return to estrus within 2 to 4 days in most cases and ovulate 8 to 12 days after treatment. This procedure may be utilized as an aid to scheduling the use of stallions.
2. Difficult-to-Breed Mares: In extended diestrus there is failure to exhibit regular estrous cycles which is different from true anestrus. Many mares described as anestrus during the breeding season have serum progesterone levels consistent with the presence of a functional corpus luteum. A proportion of “barren”, maiden, and lactating mares do not exhibit regular estrous cycles and may be in extended diestrus. Following abortion, early fetal death and resorption, or as a result of “pseudopregnancy”, there may be serum progesterone levels consistent with a functional corpus luteum. Treatment of such mares with ProstaMate usually results in regression of the corpus luteum followed by estrus and/or ovulation. Treatment of “anestrous” mares which abort subsequent to 36 days of pregnancy may not result in return to estrus due to presence of functional endometrial cups.

WARNINGS AND PRECAUTIONS

User Safety: Not for human use. Keep out of the reach of children. Women of childbearing age, asthmatics, and persons with bronchial and other respiratory problems should exercise extreme caution when handling this product. In the early stages, women may be unaware of their pregnancies. Dinoprost tromethamine is readily absorbed through the skin and can cause abortion and/or bronchiospasms. Accidental spillage on the skin should be washed off immediately with soap and water.

Contact Information: To report adverse reactions call Bimeda, Inc. at 1-888-524-6332.

Residue Warnings: No milk discard or preslaughter drug withdrawal period is required for labeled uses in cattle. No preslaughter drug withdrawal period is required for labeled uses in swine. Use of this product in excess of the approved dose may result in drug residues. Do not use in horses intended for human consumption.

Animal Safety Warnings: Severe localized clostridial infections associated with injection of ProstaMate have been reported. In rare instances, such infections have resulted in death.

Aggressive antibiotic therapy should be employed at the first sign of infection at the injection site whether localized or diffuse. Do not administer intravenously (IV) as this route may potentiate adverse reactions. Non-steroidal anti-inflammatory drugs may inhibit prostaglandin synthesis; therefore this class of drugs should not be administered concurrently. Do not administer to pregnant cattle, unless abortion is desired. Cattle administered a progestin would be expected to have a reduced response to ProstaMate. Do not administer to sows and/or gilts prior to 3 days of normal predicted farrowing as an increased number of stillbirths and postnatal mortality may result. In mares, ProstaMate is ineffective when administered prior to day-5 after ovulation.

Mare pregnancy status should be determined prior to treatment since dinoprost tromethamine injection has been reported to induce abortion and parturition when sufficient doses were administered. Mares should not be treated if they suffer from either acute or subacute disorders of the vascular system, gastrointestinal tract, respiratory system, or reproductive tract.

ADVERSE REACTIONS

Cattle: Limited salivation has been reported in some instances.

Swine: The most frequently observed side effects were erythema and pruritus, slight incoordination, nesting behavior, itching, urination, defecation, abdominal muscle spasms, tail movements, hyperpnea or dyspnea, increased vocalization, salivation, and at the 100 mg (10x) dose only, possible vomiting. These side effects are transitory, lasting from 10 minutes to 3 hours, and were not detrimental to the health of the animal.

Mares: The most frequently observed side effects are sweating and decreased rectal temperature. However, these have been transient in all cases observed and have not been detrimental to the animal.

Other reactions seen have been increase in heart rate, increase in respiration rate, some abdominal discomfort, locomotor incoordination, and lying down. These effects are usually seen within 15 minutes of injection and disappear within one hour. Mares usually continue to eat during the period of expression of side effects. One anaphylactic reaction of several hundred mares treated with dinoprost tromethamine injection was reported but was not confirmed.

CONTACT INFORMATIONTo report suspected adverse events, for technical assistance or to obtain a copy of the Safety Data Sheet (SDS) contact Bimeda, Inc. at 1-888-524-3222. For additional information about adverse drug experience reporting for animal drugs, contact FDA at 1-888-FDA-VETS or online at www.fda.gov/reportanimalae.

CLINICAL PHARMACOLOGY

General Biologic Activity: Prostaglandins occur in nearly all mammalian tissues. Prostaglandins, especially PGE’s and PGF’s, have been shown, in certain species, to 1) increase at time of parturition in amniotic fluid, maternal placenta, myometrium, and blood, 2) stimulate myometrial activity, and 3) to induce either abortion or parturition. Prostaglandins, especially PGF2α, have been shown to 1) increase in the uterus and blood to levels similar to levels achieved by exogenous administration which elicited luteolysis, 2) be capable of crossing from the uterine vein to the ovarian artery (sheep), 3) be related to IUD induced luteal regression (sheep), and 4) be capable of regressing the corpus luteum of most mammalian species studied to date. Prostaglandins have been reported to result in release of pituitary tropic hormones. Data suggest prostaglandins, especially PGE’s and PGF’s, may be involved in the process of ovulation and gamete transport. Also PGF2α has been reported to cause increase in blood pressure, bronchoconstriction, and smooth muscle stimulation in certain species.

Metabolism: A number of metabolism studies have been done in laboratory animals. The metabolism of tritium labeled dinoprost (^3H PGF2 alpha) in the rat and in the monkey was similar.

Although quantitative differences were observed, qualitatively similar metabolites were produced. A study demonstrated that equimolar doses of ^3H PGF2 alpha Tham and ^3H PGF2 alpha free acid administered intravenously to rats demonstrated no significant differences in blood concentration of dinoprost. An interesting observation in the above study was that the radioactive dose of ^3H PGF2 alpha rapidly distributed in tissues and dissipated in tissues with almost the same curve as it did in the serum. The half-life of dinoprost in bovine blood has been reported to be on the order of minutes. A complete study on the distribution of decline of ^3H PGF2 alpha Tham in the tissue of rats was well correlated with the work done in the cow. Cattle serum collected during 24 hours after doses of 0 to 250 mg dinoprost have been assayed by RIA for dinoprost and the 15-keto metabolites. These data support previous reports that dinoprost has a halflife of minutes. Dinoprost is a natural prostaglandin. All systems associated with dinoprost metabolism exist in the body; therefore, no new metabolic, transport, excretory, binding or other systems need be established by the body to metabolize injected dinoprost.

TARGET ANIMAL SAFETY

Laboratory Animals

Dinoprost was non-teratogenic in rats when administered orally at 1.25, 3.2, 10.0 and 20.0 mg dinoprost/kg/day from day 6th-15th of gestation or when administered subcutaneously at 0.5 and 1.0 mg/kg/day on gestation days 6, 7 and 8 or 9, 10 and 11 or 12, 13 and 14. Dinoprost was non-teratogenic in the rabbit when administered either subcutaneously at doses of 0.5 and 1.0 mg dinoprost/kg/day on gestation days 6, 7 and 8 or 9, 10 and 11 or 12, 13 and 14 or 15, 16 and 17 or orally at doses of 0.01, 0.1 and 1.0 mg dinoprost/ kg/day on days 6-18 or 5.0 mg/kg/day on days 8-18 of gestation. A slight and marked embryo lethal effect was observed in dams given 1.0 and 5.0 mg dinoprost/kg/day respectively. This was due to the expected luteolytic properties of the drug.

A 14-day continuous intravenous infusion study in rats at 20 mg PGF2α per kg body weight indicated prostaglandins of the F series could induce bone deposition. However, such bone changes were not observed in monkeys similarly administered dinoprost tromethamine injection at 15 mg dinoprost per kg body weight for 14 days.

Cattle

In cattle, evaluation was made of clinical observations, clinical chemistry, hematology, urinalysis, organ weights, and gross plus microscopic measurements following treatment with various doses up to 250 mg dinoprost administered twice intramuscularly at a 10 day interval or doses of 25 mg administered daily for 10 days. There was no unequivocal effect of dinoprost on the hematology or clinical chemistry parameters measured. Clinically, a slight transitory increase in heart rate was detected. Rectal temperature was elevated about 1.5˚ F through the 6th hour after injection with 250 mg dinoprost, but had returned to baseline at 24 hours after injection. No dinoprost associated gross lesions were detected. There was no evidence of toxicological effects. Thus, dinoprost had a safety factor of at least 10X on injection (25 mg luteolytic dose vs. 250 mg safe dose), based on studies conducted with cattle. At luteolytic doses, dinoprost had no effect on progeny. If given to a pregnant cow, it may cause abortion; the dose required for abortion varies considerably with the stage of gestation. Induction of abortion in feedlot cattle at stages of gestation up to 100 days of gestation did not result in dystocia, retained placenta or death of heifers in the field studies. The smallness of the fetus at this early stage of gestation should not lead to complications at abortion. However, induction of parturition or abortion with any exogenous compound may precipitate dystocia, fetal death, retained placenta and/or metritis, especially at latter stages of gestation.

Swine

In pigs, evaluation was made of clinical observations, food consumption, clinical pathologic determinations, body weight changes, urinalysis, organ weights, and gross and microscopic observations following treatment with single doses of 10, 30, 50 and 100 mg dinoprost administered intramuscularly. The results indicated no treatment related effects from dinoprost treatment that were deleterious to the health of the animals or to their offspring.

Mares

Dinoprost tromethamine was administered to adult mares (weighing 320 to 485 kg; 2 to 20 years old), at the rates of 0, 100, 200, 400, and 800 mg per mare per day for 8 days. Route of administration for each dose group was both intramuscularly (2 mares) and subcutaneously (2 mares). Changes were detected in all treated groups for clinical (reduced sensitivity to pain; locomotor incoordination; hypergastromotility; sweating; hyperthermia; labored respiration), blood chemistry (elevated cholesterol, total bilirubin, LDH, and glucose), and hematology (decreased eosinophils; increased hemoglobin, hematocrit, and erythrocytes) measurements. The effects in the 100 mg dose, and to a lesser extent, the 200 mg dose groups were transient in nature, lasting for a few minutes to several hours. Mares did not appear to sustain adverse effects following termination of the side effects.

Mares treated with either 400 mg or 800 mg exhibited more profound symptoms. The excessive hyperstimulation of the gastrointestinal tract caused a protracted diarrhea, slight electrolyte imbalance (decreased sodium and potassium), dehydration, gastrointestinal irritation, and slight liver malfunction (elevated SGOT, SGPT at 800 mg only). Heart rate was increased but pH of the urine was decreased. Other measurements evaluated in the study remained within normal limits. No mortality occurred in any of the groups. No apparent differences were observed between the intramuscular and subcutaneous routes of administration. Luteolytic doses of dinoprost tromethamine are on the order of 5 to 10 mg administered on one day, therefore, dinoprost tromethamine injection was demonstrated to have a wide margin of safety. Thus, the 100 mg dose gave a safety margin of 10 to 20X for a single injection or 80 to 160X for the 8 daily injections.

Additional studies investigated the effects in the mare of single intramuscular doses of 0, 0.25, 1.0, 2.5, 3.0, 5.0, and 10.0 mg dinoprost tromethamine. Heart rate, respiration rate, rectal temperature, and sweating were measured at 0, 0.25, 0.50, 0.75, 1.0, 1.5, 2.0, 3.0, 4.0, 5.0, and 6.0 hr. after injection. Neither heart rate nor respiration rates were significantly altered (P > 0.05) when compared to contemporary control values. Sweating was observed for 0 of 9, 2 of 9, 7 of 9, 9 of 9, and 8 of 9 mares injected with 0.25, 1.0, 2.5, 3.0, 5.0, or 10.0 mg dinoprost tromethamine, respectively. Sweating was temporary in all cases and was mild for doses of 3.0 mg or less but was extensive (beads of sweat over the entire body and dripping) for the 10 mg dose. Sweating after the 5.0 mg dose was intermediate between that seen for mares treated with 3.0 and 10.0 mg. Sweating began within 15 minutes after injection and ceased by 45 to 60 minutes after injection. Rectal temperature was decreased during the interval 0.5 until 1.0, 3 to 4, or 5 hours after injection for 0.25 and 1.0 mg, 2.5 and 3.0, or 5.0 and 10.0 mg dose groups, respectively. Average rectal temperature during the periods of decreased temperature was on the order of 97.5 to 99.6, with the greatest decreases observed in the 10 mg dose group.

SUMMARY OF SAFETY AND EFFECTIVENESS

EFFECTIVESS

Cattle:

For Treatment of Pyometra (chronic endometritis) in Cattle: In studies conducted with dinoprost tromethamine injection, pyometra was defined as presence of a corpus luteum in the ovary and uterine horns containing fluid but not a conceptus based on palpation per rectum. Return to normal was defined as evacuation of fluid and return of the uterine horn size to 40mm or less based on palpation per rectum at 14 and 28 days. Most cattle that recovered in response to dinoprost tromethamine injection recovered within 14 days after injection. After 14 days, recovery rate of treated cattle was no different than that of non-treated cattle.

For Abortion in Beef Cows, Beef Heifers and Replacement Dairy Heifers: Commercial cattle were palpated per rectum for pregnancy in six feedlots. The percent of pregnant cattle in each feedlot less than 100 days of gestation ranged between 26 and 84; 80% or more of the pregnant cattle were less than 150 days of gestation. The abortion rates following injection of dinoprost tromethamine injection increased with increasing doses up to about 25 mg. As examples, the abortion rates, over 7 feedlots on the dose titration study, were 22%, 50%, 71%, 90% and 78% for cattle up to 100 days of gestation when injected IM with dinoprost tromethamine injection doses of 0, 1 (5 mg), 2 (10 mg), 4 (20 mg) and 8 (40 mg) mL, respectively. The statistical predicted relative abortion rate based on the dose titration data, was about 93% for the 5 mL (25 mg) dinoprost tromethamine injection dose for cattle injected up to 100 days of gestation.

For use with gonadorelin injection to synchronize estrous cycles to allow fixed time artificial insemination (FTAI) in lactating dairy cows: For a full description of the studies conducted for the use of gonadorelin injection and dinoprost tromethamine injection, please refer to the labeling for gonadorelin injection.

Mares:

For Difficult-to-Breed Mares: In one study with 122 Standardbred and Thoroughbred mares in clinical anestrus for an average of 58 days and treated during the breeding season, behavioral estrus was detected in 81 percent at an average time of 3.7 days after injection with 5 mg dinoprost tromethamine injection; ovulation occurred an average of 7.0 days after treatment. Of those mares bred, 59% were pregnant following an average of 1.4 services during that estrus.

HOW SUPPLIED

ProstaMate is available in 90 mL vials.

STORAGE CONDITIONS

Store at controlled room temperature 20° to 25°C (68° to 77°F).
Use within 3 months of first puncture and puncture a maximum of 20 times with a needle or 5 times with a dosage delivery device. When using a draw-off spike or needle with bore diameter larger than 4.90 mm, discard any product remaining in the vial immediately after use. Protect from freezing.

Approved by FDA under ANADA # 200-253

Restricted Drug (California) – Use Only as Directed
ProstaMate® is a registered trademark of Bimeda, Inc.
Manufactured for:
Bimeda, Inc.

Le Sueur, MN 56058
www.bimeda.com

Revised: 10/21